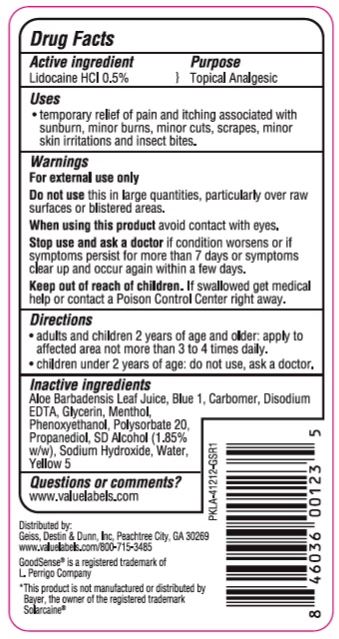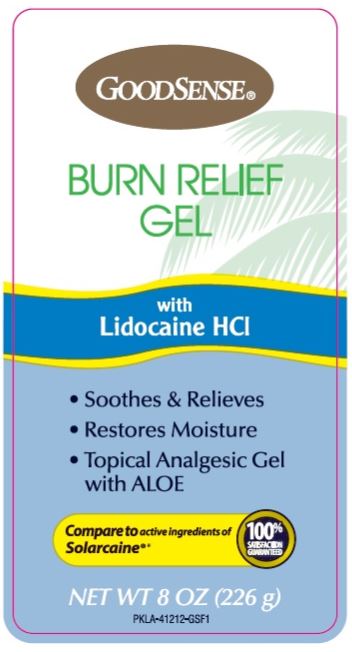 DRUG LABEL: GoodSense Burn Relief Gel
NDC: 70281-618 | Form: GEL
Manufacturer: Solskyn Personal Care LLC
Category: otc | Type: HUMAN OTC DRUG LABEL
Date: 20190628

ACTIVE INGREDIENTS: LIDOCAINE HYDROCHLORIDE 0.5 g/100 g
INACTIVE INGREDIENTS: ALCOHOL; WATER; ALOE VERA LEAF; FD&C BLUE NO. 1; EDETATE DISODIUM; GLYCERIN; MENTHOL; PHENOXYETHANOL; POLYSORBATE 20; PROPANEDIOL; SODIUM HYDROXIDE; BASIC YELLOW 5

GoodSense Burn Relief Gel

Active Ingredients

Lidocaine 0.5%

Purpose

Topical Analgesic

Uses

- tempory relief of pain and itching associated with sunburn, minor burns, minor cuts, scrapes, minor skin irritations, and insect bites.

Dosage & Administration

For temporary relief of itching associated with minor skin irritations and rashes due to eczema, insect bites, and poison oak.

Warnings

For external use only

Do not use this in large quantities, particularly over raw surfaces or blistered areas.

When using this product avoid contact with the eyes.

Stop use and ask a doctor

if condition worsens or if symptoms persist for more than 7 days or symptoms clear up and occur again within a few days.

Keep out of reach of children.

If swallowed get medical help or contact a Poison Control Center right away.

Directions

- adults and children 2 years of age and older: apply to affected area not more than 3 to 4 times daily.
- children under 2 years of age: do not use, ask a doctor.

Inactive Ingredients

Aloe Barbadensis Leaf Juice, Blue 5, Carbomer. Disodium, EDTA Glycerin, Menthol, Phenoxyethanol, Polysorbate 20, Propanediol, SD Alcohol (1.85% w/w). Sodium Hydroxide, Water, Yellow 5

Questions or Comments?

www.valuelabels.com

Principal Display Panel

GOODSENSE

BURN RELIEF

GEL

with

Lidocaine HCl

- Soothes & Relieves
- Restores Moisture
- Topical Analgesic Gel

with ALOE

Compare to active ingredients of

Solarcaine

100% satisfaction guaranteed

NET WT 8 OZ (226 g)

PKLA-41212-GSF1